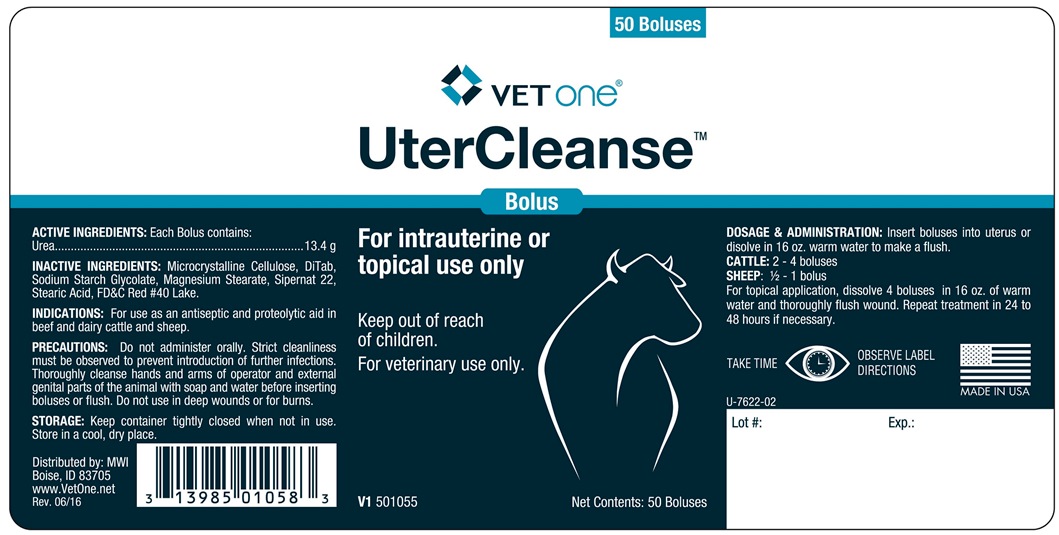 DRUG LABEL: UterCleanse
NDC: 13985-588 | Form: TABLET
Manufacturer: MWI/Vet One
Category: animal | Type: OTC ANIMAL DRUG LABEL
Date: 20180423

ACTIVE INGREDIENTS: UREA 13 g/1 1

UterCleanse

INDICATIONS AND USAGE

For intrauterine or topical use only

Keep out or reach of children.

For veterinary use only.

INDICATIONS

For use as an antiseptic and proteolytic aid in beef and dairy cattle and sheep.

COMPONENTS

ACTIVE INGREDIENTS: Each Bolus contains:

Urea ..................... 13.4 g

INACTIVE INGREDIENTS: Microcrystalline Cellulose, DiTab, Sodium Starch Glycolate, Magnesium Stearate, Sipernat 22, Stearic Acid, FD&C Red #40 Lake.

PRECAUTIONS

Do not administer orally. Strict cleanliness must be observed to prevent introduction of further infections. Thoroughly cleanse hands and arms of operator and external genital parts of the animal with soap and water before inserting boluses or flush. Do not use in deep wounds or for burns.

STORAGE

Keep container tightly closed when not in use. Store in a cool, dry place.

DOSAGE AND ADMINISTRATION

Insert boluses into uterus or dissolve in 16 oz. warm water and make a flush.

Cattle: 2 - 4 boluses

SHEEP: 1/2 - 1 bolus

For topical application, dissolve 4 boluses in 16 oz. of warm water and thoroughly flush wound. Repeat treatment in 24 to 48 hours, if necessary.

TAKE TIME OBSERVE LABEL DIRECTIONS